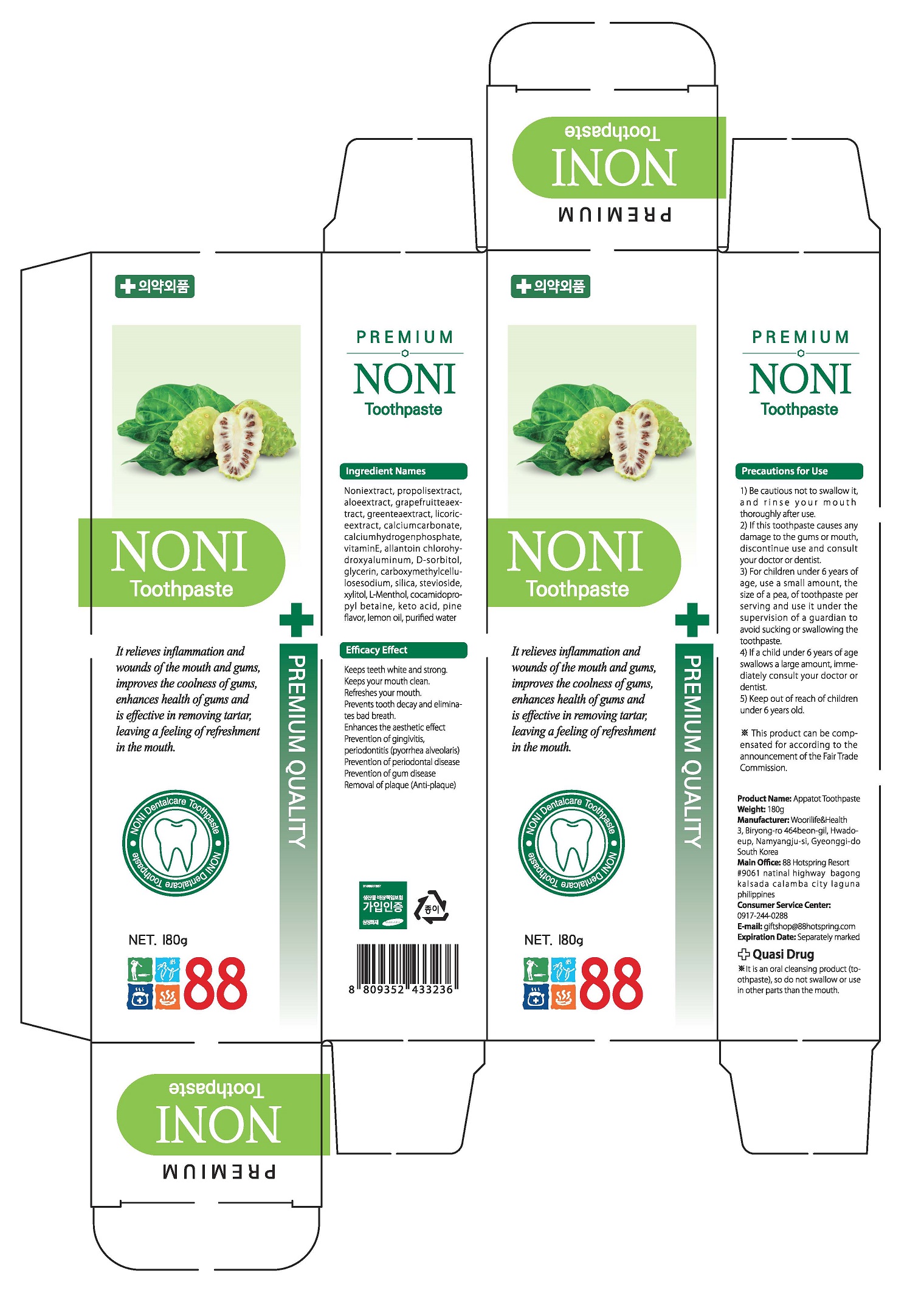 DRUG LABEL: AppatotToothpaste
NDC: 73065-0011 | Form: PASTE, DENTIFRICE
Manufacturer: WOORI LIFE & HEALTH
Category: otc | Type: HUMAN OTC DRUG LABEL
Date: 20240116

ACTIVE INGREDIENTS: CALCIUM CARBONATE 0.1 g/100 g
INACTIVE INGREDIENTS: .ALPHA.-TOCOPHEROL ACETATE; PEPPERMINT OIL; XYLITOL; WATER

ACTIVE INGREDIENT

Calcium Carbonate

PURPOSE

Tooth whitening, tooth decay prevention, bad breath removal. Makes tooth strong.

Keeps the mouth clean, Refreshes the inside of the mouth. lncreases the aesthetic effect. Prevention of periodontal disease, gum disease and, removal of plaque (anti-plaque)

Keep out of reach of children

INDICATIONS AND USAGE

apply appropriate amount of the tooth paste on the tooth brush and brush the teeth

WARNINGS

(1) Do not swallow, gargle fully after using.
(2) If the use of this paste causes gingiva or oral cavity injury, please stop using and consult a doctor or a dentist.
(3) If childern under 6 years of age use, please apply a pea-sized amount each thime. Do not swallow. Please use under the guidance of the guardian.
(4) If children under 6 years of age accidentally ingest large amounts of the paste, please consult a doctor or a dentist immediately.
(5) Keep out of reach of children under 6 years of age.

INACTIVE INGREDIENT

Tocopheryl Acetate
Aluminum Chlorohydroxy Allantoinate
Dibasic Calcium Phosphate Hydrate
D-Sorbitol Solution
Glycerin
Silica
Carboxymethylcellulose Sodium
Chitosan
Cocamidopropyl Betaine
Steviol Glycoside
Xylitol
L-Menthol
Aloe Extract(09)
Grapefruit Seed Extract
Green Tea Extract
Glycyrrhiza Extract
Morinda Citrifolia Extract
Sage Extract
Propolis Extract
Lemon oil
Peppermint Oil
Pine fravor
Activated carbon
Hydroxyapatite
Purified Water in Bulk

DOSAGE AND ADMINISTRATION

For dental use only